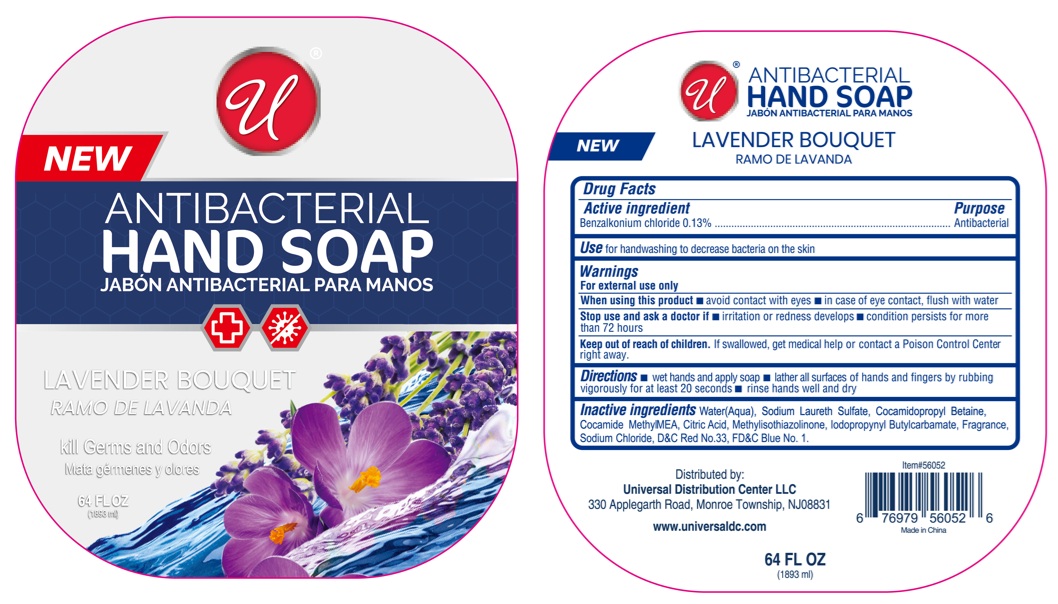 DRUG LABEL: ANTIBACTERIAL LAVENDER BOUQUET
NDC: 52000-435 | Form: LIQUID
Manufacturer: Universal Distribution Center LLC
Category: otc | Type: HUMAN OTC DRUG LABEL
Date: 20251229

ACTIVE INGREDIENTS: BENZALKONIUM CHLORIDE 0.13 g/100 mL
INACTIVE INGREDIENTS: WATER; SODIUM LAURETH-3 SULFATE; COCAMIDOPROPYL BETAINE; COCOYL METHYL MONOETHANOLAMINE; CITRIC ACID MONOHYDRATE; METHYLISOTHIAZOLINONE; IODOPROPYNYL BUTYLCARBAMATE; SODIUM CHLORIDE; D&C RED NO. 33; FD&C BLUE NO. 1

ANTIBACTERIAL HAND SOAP LAVENDER BOUQUET

Active ingredient

Benzalkonium chloride 0.13%

Purpose

Antibacterial

Use

for handwashing to decrease bacteria on the skin

Warnings

For external use only

When using this product • avoid contact with eyes • in case of eye contact, flush with water

Stop use and ask a doctor if • irritation or redness develops • condition persists for more than 72 hours

Keep out of reach of children. If swallowed, get medical help or contact a Poison Control Center right away.

Directions

• wet hands and apply soap • lather all surfaces of hands and fingers by rubbing vigorously for at least 20 seconds • rinse hands well and dry

Inactive ingredients

Water(Aqua), Sodium Laureth Sulfate, Cocamidopropyl Betaine, Cocamide Methyl MEA, Citric Acid, Methylisothiazolinone, Iodopropynyl Butylcarbamate, Fragrance, Sodium Chloride, D&C Red No. 33, FD&C Blue No. 1.

NEW

kill Germs and Odors

Distributed by:
Universal Distribution Center LLC
330 Applegarth Road, Monroe Township, NJ08831

www.universaldc.com

Made in China